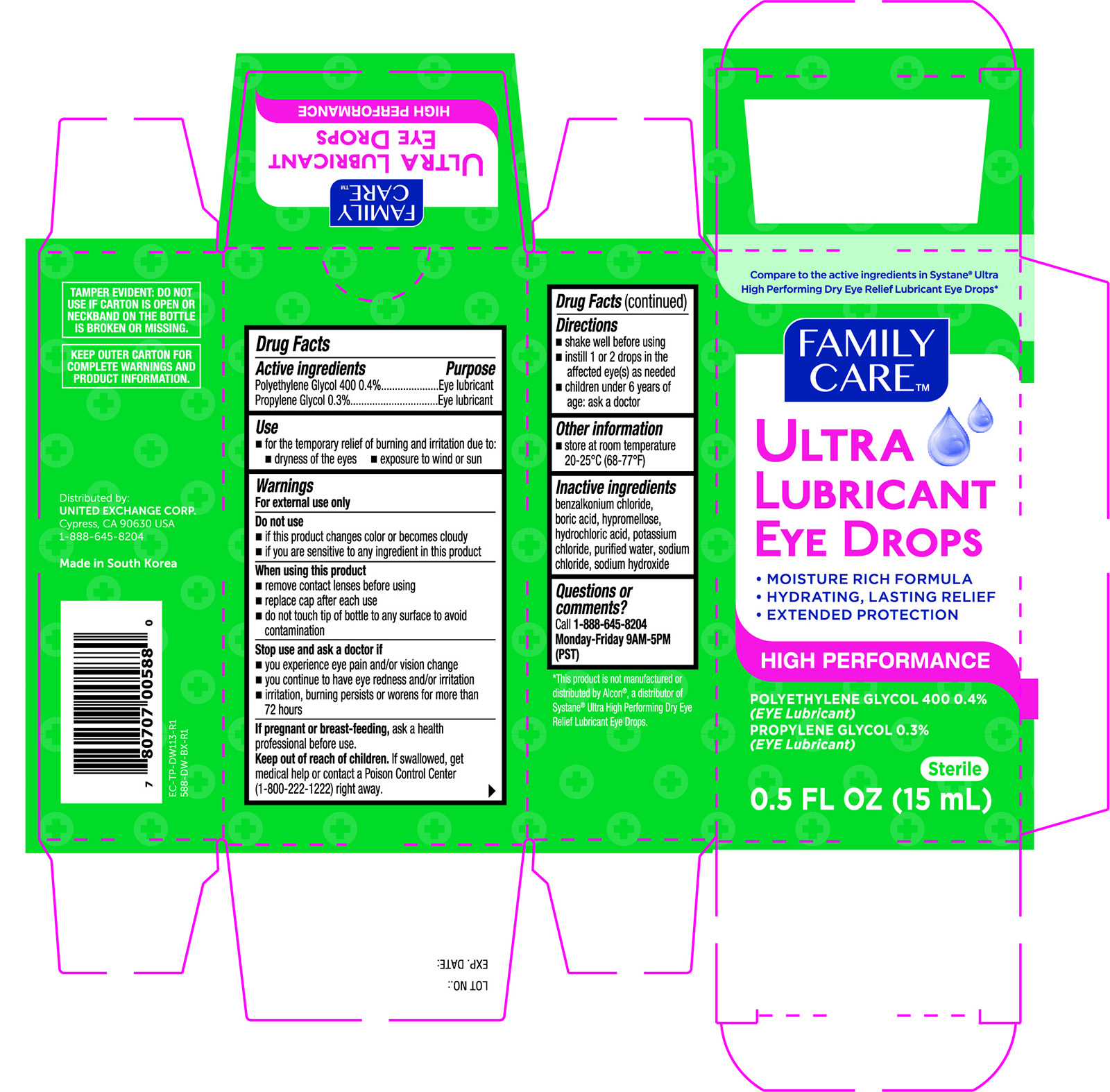 DRUG LABEL: Family Care Ultra Lubricant
NDC: 65923-588 | Form: SOLUTION/ DROPS
Manufacturer: United Exchange Corp.
Category: otc | Type: HUMAN OTC DRUG LABEL
Date: 20251031

ACTIVE INGREDIENTS: POLYETHYLENE GLYCOL 400 4 mg/1 mL; PROPYLENE GLYCOL 3 mg/1 mL
INACTIVE INGREDIENTS: HYPROMELLOSE, UNSPECIFIED; HYDROCHLORIC ACID; WATER; BORIC ACID; BENZALKONIUM CHLORIDE; POTASSIUM CHLORIDE; SODIUM CHLORIDE; SODIUM HYDROXIDE

Family Care Ultra Lubricant Eye Drops 588 (NBE Systane Ultra)

Drug Facts

Active ingredients Purpose

Polyethylene Glycol 400 0.4%....................... Eye lubricant

Propylene Glycol 0.3%....................................Eye lubricant

Uses

- for the temporary relief of burning and irritation due to:
- dryness of the eyes
- exposure to wind or sun

Warnings

For external use only

Do not use

- if this product changes color or becomes cloudy
- if you are sensitive to any ingredient is this product

When using this product

- remove contact lenses before use
- replace cap after each use
- do not touch tip of bottle to any surface to avoid contamination

Stop use and ask a doctor if

- you experience eye pain and/or vision change
- you continue to have eye redness and/or irritation
- irritation, burning persists or worsens for more than 72 hours

PREGNANCY OR BREAST FEEDING

If pregnant or breast-feeding, ask a health professional before use.

Keep out of reach of children. If swallowed, get medical help or contact a Poison Control Center (1-800-222-1222) right away.

Directions

- shake well before using
- instill 1 or 2 drops in the affected eye(s) as needed
- children under 6 years of age: ask a doctor

Inactive ingredients

benzalkonium chloride, boric acid, hypromellose, hydrochloric acid, potassium chloride, purified water, sodium chloride, sodium hydroxide

DOSAGE AND ADMINISTRATION

Distributed by:

United Exchange Corp,

Cypress, CA 90630 USA

1-888-645-8204

Made in South Korea